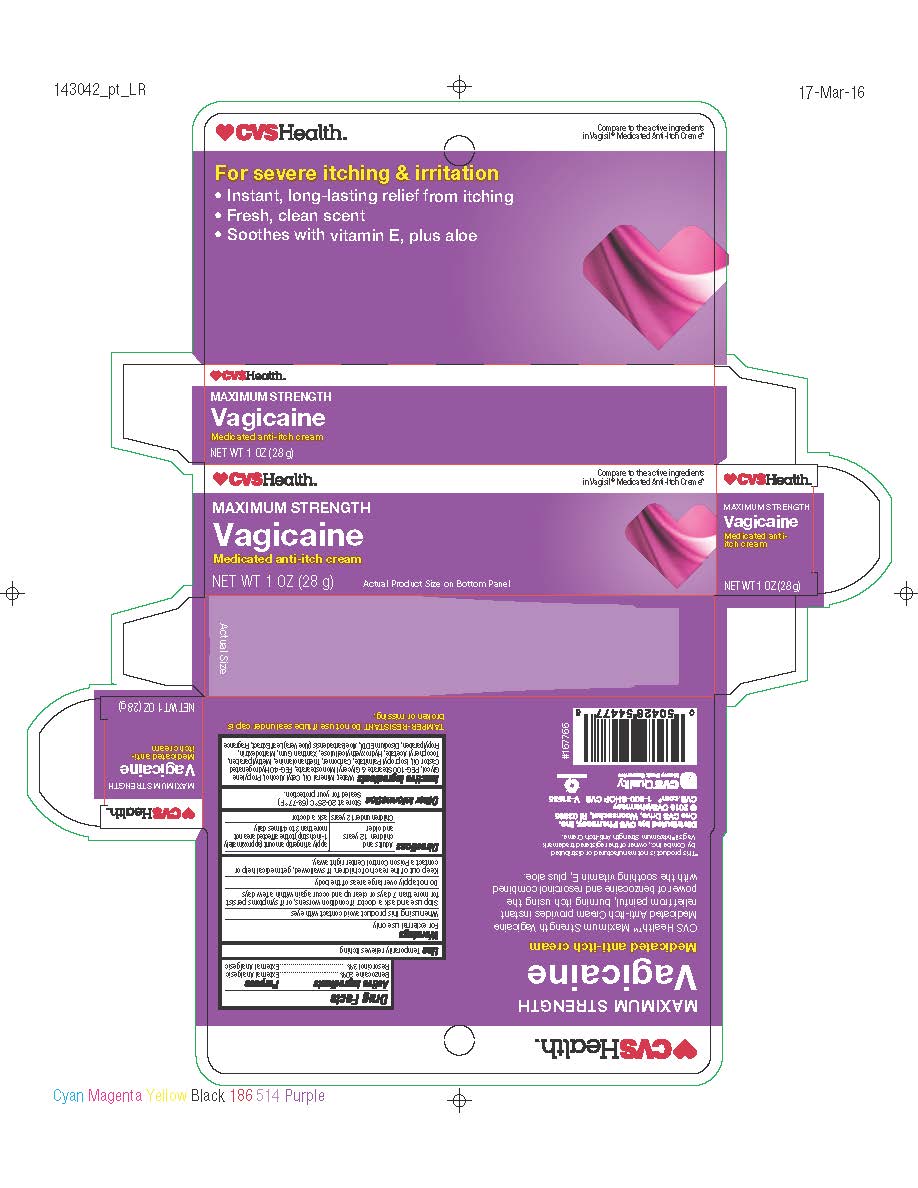 DRUG LABEL: Vagicaine Maximum Strength Anti-Itch Cream
NDC: 59779-588 | Form: CREAM
Manufacturer: CVS Pharmacy
Category: otc | Type: HUMAN OTC DRUG LABEL
Date: 20160418

ACTIVE INGREDIENTS: BENZOCAINE 5.6 g/28 g; RESORCINOL 0.84 g/28 g
INACTIVE INGREDIENTS: CETYL ALCOHOL; PROPYLENE GLYCOL; PEG-100 STEARATE; GLYCERYL MONOSTEARATE; PEG-40 HYDROGENATED LANOLIN; ISOPROPYL PALMITATE; CARBOMER HOMOPOLYMER TYPE C; TROLAMINE; METHYLPARABEN; .ALPHA.-TOCOPHEROL ACETATE; HYDROXYETHYL CELLULOSE (1500 MPA.S AT 1%); XANTHAN GUM; MALTODEXTRIN; PROPYLPARABEN; EDETATE DISODIUM; ALOE VERA LEAF; MINERAL OIL; WATER

Drug Facts

Active Ingredients

Benzocaine 20%

Resorcinol 3%

Purpose

External Analgesic

External Analgesic

INDICATIONS AND USAGE

Temporarily relieves itching

Warnings

For external use only

When using this product avoid contact with the eyes

Stop use and ask doctor if condition worsens, or if symptoms persist for more than 7 days or clear up and occur again within a few days.

DO NOT USE

Do not apply over large areas of the body

Keep out of reach of children. If swallowed, get medical help or contact a Poison Control Center right away.

Directions

adults and children 12 years and older | apply a fingertip amount (appriximately 1-inch strip) to the affected area not more than 3 to 4 times daily
children under 12 years | ask a doctor

Other Information

- store at 20º-25ºC (68º - 77ºF)

Inactive Ingredients

Water, Mineral Oil, Cetyl Alcohol, Propylene Glycol, PEG-100 Stearate and Glyceryl Monostearate, PEG-40 Hydrogenated Castor Oil, Isopropyl Palmitate, Carbomer, Triethanolamine, Methylparaben, Tocopheryl Acetate, Hydroxyethylcelluse, Xanthan Gum, Maltodextrin, Propylparaben, Disodium EDTA, Aloe Barbadensis (Alow Vera) Leaf Extract, Fragrance

PACKAGE LABEL

Maximum Strength

Vagicaine

Medicated anti-itch cream

Net Wt 1 oz (28g)

CVS HealthTM Maximum Strength Vagicaine Medicaided Anti-Itch Cream provides instant relief from painful, burning itch using the power of benzocaine and resorcinol combined with the soothing vitamin E plus aloe.

*This product is not manufactured or distributed by Combe Inc., owner of the registered trademark VagisilTM maximum Strength Anti-Itch Cream

Distributed by: CVS Pharmacy, Inc.

One CVS Drive, Woonsocket, RI 02995

(c) 2016 CVS/pharmacy

CVS.com(R) 1-800-SHOP CVS V-31535

CVS(R) Quality

Money Back Guarantee